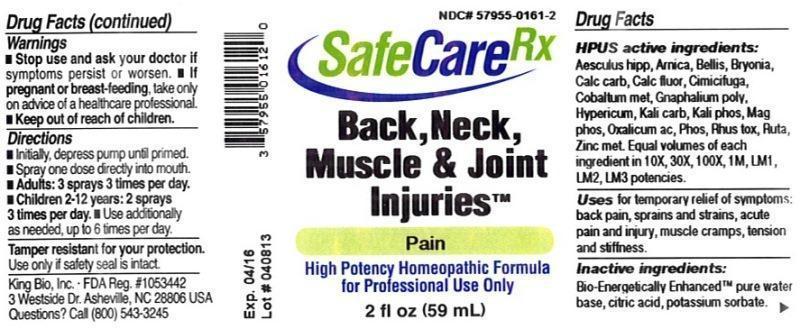 DRUG LABEL: Back, Neck, Muscle and Joint Injuries
NDC: 57955-0161 | Form: LIQUID
Manufacturer: King Bio Inc.
Category: homeopathic | Type: HUMAN OTC DRUG LABEL
Date: 20140417

ACTIVE INGREDIENTS: HORSE CHESTNUT 10 [hp_X]/59 mL; ARNICA MONTANA 10 [hp_X]/59 mL; BELLIS PERENNIS 10 [hp_X]/59 mL; BRYONIA ALBA ROOT 10 [hp_X]/59 mL; OYSTER SHELL CALCIUM CARBONATE, CRUDE 10 [hp_X]/59 mL; CALCIUM FLUORIDE 10 [hp_X]/59 mL; BLACK COHOSH 10 [hp_X]/59 mL; COBALT 10 [hp_X]/59 mL; PSEUDOGNAPHALIUM OBTUSIFOLIUM 10 [hp_X]/59 mL; HYPERICUM PERFORATUM 10 [hp_X]/59 mL; POTASSIUM CARBONATE 10 [hp_X]/59 mL; POTASSIUM PHOSPHATE, DIBASIC 10 [hp_X]/59 mL; MAGNESIUM PHOSPHATE, DIBASIC TRIHYDRATE 10 [hp_X]/59 mL; OXALIC ACID DIHYDRATE 10 [hp_X]/59 mL; PHOSPHORUS 10 [hp_X]/59 mL; TOXICODENDRON PUBESCENS LEAF 10 [hp_X]/59 mL; RUTA GRAVEOLENS FLOWERING TOP 10 [hp_X]/59 mL; ZINC 10 [hp_X]/59 mL
INACTIVE INGREDIENTS: WATER; CITRIC ACID MONOHYDRATE; POTASSIUM SORBATE

Back, Neck, Muscle and Joint Injuries™

ACTIVE INGREDIENT

Drug Facts__________________________________________________________________________________________________________

HPUS active ingredients: Aesculus hippocastanum, Arnica montana, Bellis perennis, Bryonia, Calcarea carbonica, Calcarea fluorica, Cimicifuga racemosa, Cobaltum metallicum, Gnaphalium polycephalum, Hypericum perforatum, Kali carbonicum, Kali phosphoricum, Magnesia phosphorica, Oxalicum acidum, Phosphorus, Rhus toxicodendron, Ruta Graveolens, Zincum metallicum. Equal volumes of each ingredient in 10X, 30X, 100X, 1M, LM1, LM2, LM3 potencies.

INDICATIONS AND USAGE

Uses for temporary relief of symptoms: back pain, sprains and strains, acute pain and injury, muscle cramps, tension and stiffness.

Inactive Ingredients:

Bio-Energetically Enhanced™ pure water, citric acid and potassium sorbate.

Warnings

- Stop use and ask your doctor if symptoms persist or worsen.
- If pregnant or breast-feeding, take only on advice of a healthcare professional.

- Keep out of reach of children.

Directions

- Initially, depress pump until primed.
- Spray one dose directly into mouth.
- Adults: 3 sprays 3 times per day.
- Children 2-12 years: 2 sprays 3 times per day.
- Use additionally as needed, up to 6 times per day.

OTHER SAFETY INFORMATION

Tamper resistant for your protection. Use only if safety seal is intact.

PURPOSE

Uses for temporary relief of symptoms:

- back pain
- sprains and strains
- acute pain and injury
- muscle cramps
- tension and stiffness